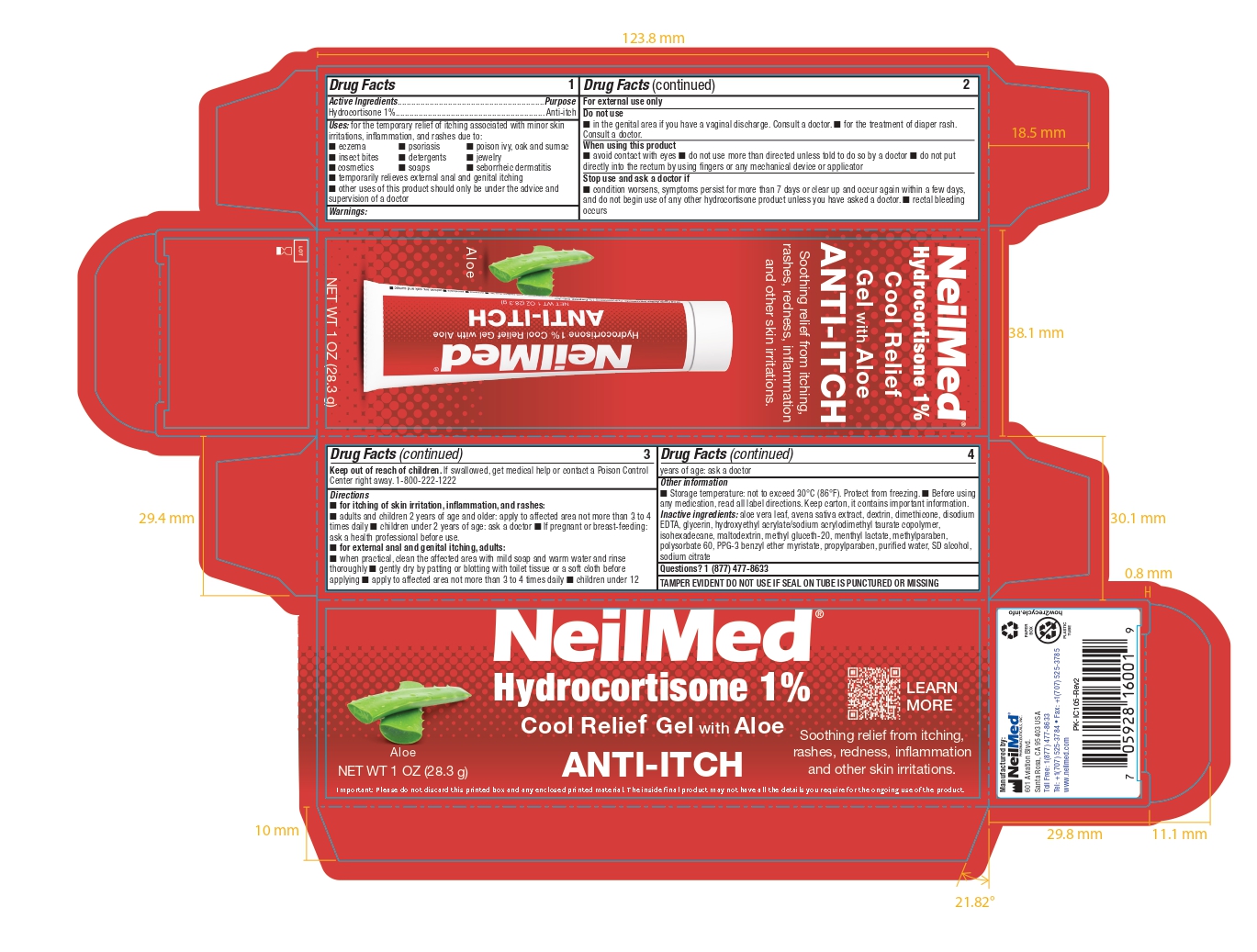 DRUG LABEL: Anti Itch
NDC: 13709-326 | Form: GEL
Manufacturer: Neilmed Pharmaceuticals Inc.
Category: otc | Type: HUMAN OTC DRUG LABEL
Date: 20240420

ACTIVE INGREDIENTS: HYDROCORTISONE 1 g/100 g
INACTIVE INGREDIENTS: ALOE VERA LEAF; AVENA SATIVA POLLEN; ICODEXTRIN; HYDROXYETHYL ACRYLATE/SODIUM ACRYLOYLDIMETHYL TAURATE COPOLYMER (45000 MPA.S AT 1%); MENTHYL LACTATE, (-)-; EDETATE DISODIUM; PPG-3 BENZYL ETHER MYRISTATE; DIMETHICONE 1000; POLYSORBATE 60; METHYLPARABEN; SODIUM CITRATE; PROPYLPARABEN; GLYCERIN; DEHYDRATED ALCOHOL; WATER; ISOHEXADECANE; MALTODEXTRIN; METHYL GLUCETH-20

Drug Facts

Active Ingredients
Hydrocortisone 1%

Drug Facts

Active Ingredients....................................................Purpose
Hydrocortisone 1%..................................................... Anti-itch

Uses

Uses: for the temporary relief of itching associated with minor skin irritations, inflammation, and rashes due to:
■ eczema
■ insect bites
■ cosmetics
■ psoriasis
■ detergents
■ soaps
■ poison ivy, oak and sumac
■ jewelry
■ seborrheic dermatitis

■ temporarily relieves external anal and genital itching
■ other uses of this product should only be under the advice and supervision of a doctor

Do not Use

- in the genital area if you have a vaginal discharge. Consult a doctor.
- for the treatment of diaper rash. Consult a doctor.

When using this product

- avoid contact with eyes
- do not use more than directed unless told to do so by a doctor
- do not put directly into the rectum by using fingers or any mechanical device or applicator

Stop use and ask a doctor if

■ condition worsens, symptoms persist for more than 7 days or clear up and occur again within a few days, and do not begin use of any other hydrocortisone product unless you have asked a doctor.

■ rectal bleeding occurs

Keep out of reach of children. If swallowed, get medical help or contact a Poison

Directions

■ for itching of skin irritation, inflammation, and rashes:
■ adults and children 2 years of age and older: apply to affected area not more than 3 to 4 times daily

■ children under 2 years of age: ask a doctor

■ If pregnant or breast-feeding: ask a health professional before use.

■ for external anal and genital itching,

adults:
■ when practical, clean the affected area with mild soap and warm water and rinse
thoroughly

■ gently dry by patting or blotting with toilet tissue or a soft cloth before
applying

■ apply to affected area not more than 3 to 4 times daily

■ children under 12 years of age: ask a doctor

Storage temperature

not to exceed 30°C (86°F).

Protect from freezing.

■ Before using any medication, read all label directions.

Keep carton, it contains important information.

Inactive ingredients:

aloe vera leaf, avena sativa extract, dextrin, dimethicone, disodium EDTA, glycerin, hydroxyethyl acrylate/sodium acrylodimethyl taurate copolymer, isohexadecane, maltodextrin, methyl gluceth-20, methyl lactate, methylparaben, polysorbate 60, PPG-3 benzyl ether myristate, propylparaben, purified water, SD alcohol,sodium citrate

SAFE HANDLING WARNING

TAMPER EVIDENT DO NOT USE IF SEAL ON TUBE IS PUNCTURED OR MISSING

Directions

for itching of skin irritation, inflammation, and rashes:
■ adults and children 2 years of age and older: apply to affected area not more than 3 to 4 times daily

■ children under 2 years of age: ask a doctor

■ If pregnant or breast-feeding: ask a health professional before use.
■ for external anal and genital itching, adults:
■ when practical, clean the affected area with mild soap and warm water and rinse thoroughly ■ gently dry by patting or blotting with toilet tissue or a soft cloth before applying ■ apply to affected area not more than 3 to 4 times daily

Warnings

For external use only.

Do not use
■ in the genital area if you have a vaginal discharge. Consult a doctor. ■ for the treatment of diaper rash.
Consult a doctor.